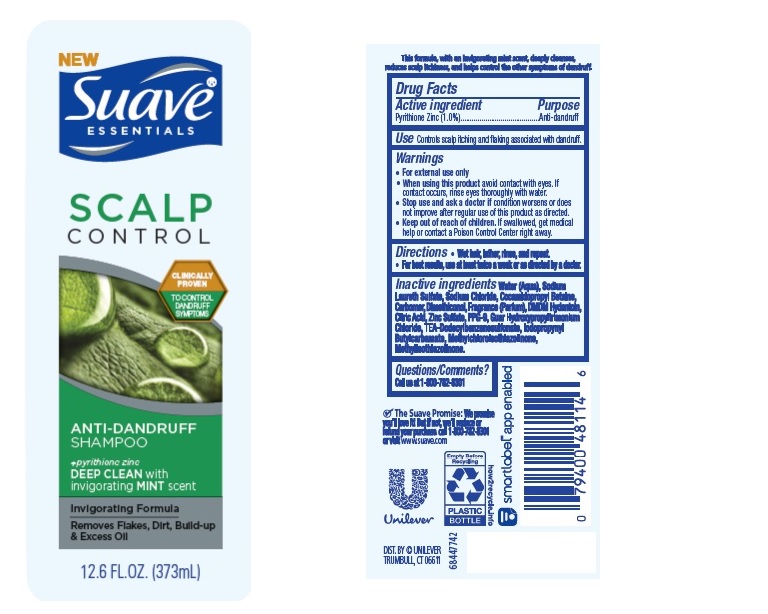 DRUG LABEL: Suave
NDC: 64942-1875 | Form: SHAMPOO
Manufacturer: Conopco, Inc. d/b/a/ Unilever
Category: otc | Type: HUMAN OTC DRUG LABEL
Date: 20221207

ACTIVE INGREDIENTS: PYRITHIONE ZINC 1 g/100 mL
INACTIVE INGREDIENTS: WATER; SODIUM LAURETH SULFATE; COCAMIDOPROPYL BETAINE; SODIUM CHLORIDE; DIMETHICONOL (40 CST); CARBOMER HOMOPOLYMER TYPE C (ALLYL PENTAERYTHRITOL CROSSLINKED); DMDM HYDANTOIN; GUAR HYDROXYPROPYLTRIMONIUM CHLORIDE (1.7 SUBSTITUENTS PER SACCHARIDE); CITRIC ACID MONOHYDRATE; ZINC SULFATE, UNSPECIFIED FORM; TRIETHANOLAMINE DODECYLBENZENESULFONATE; PPG-9; IODOPROPYNYL BUTYLCARBAMATE; METHYLCHLOROISOTHIAZOLINONE; METHYLISOTHIAZOLINONE

Suave Essentials Scalp Control Deep Clean with Invigorating Mint Anti-Dandruff Shampoo

Drug Facts

Active ingredient
Pyrithione Zinc (1.0%)

Purpose

Anti-dandruff

Use

- Controls scalp itching and flaking associated with dandruff.

Warnings

For external use only

When using this product: avoid contact with eyes. If contact occurs, rinse eyes thoroughly with water.
Stop use and ask a doctor if: condition worsens or does not improve after regular use of this product as directed.

KEEP OUT OF REACH OF CHILDREN

Keep this and all drugs out of reach of children. If swallowed, get medical help or contact a Poison Control Center right away.

Directions

Wet hair, lather, rinse, and repeat.
For best results, use at least twice a week or as directed by a doctor.

Inactive Ingredients

Water (Aqua), Sodium Laureth Sulfate, Sodium Chloride, Cocamidopropyl Betaine, Carbomer, Dimethiconol, Fragrance (Parfum), DMDM Hydantoin, Citric Acid, Zinc Sulfate, PPG-9, Guar Hydroxypropyltrimonium Chloride, TEA-Dodecylbenzenesulfonate, Iodopropynyl Butylcarbamate, Methylchloroisothiazolinone, Methylisothiazolinone.

Questions/comments?

Call us at 1-800-782-8301